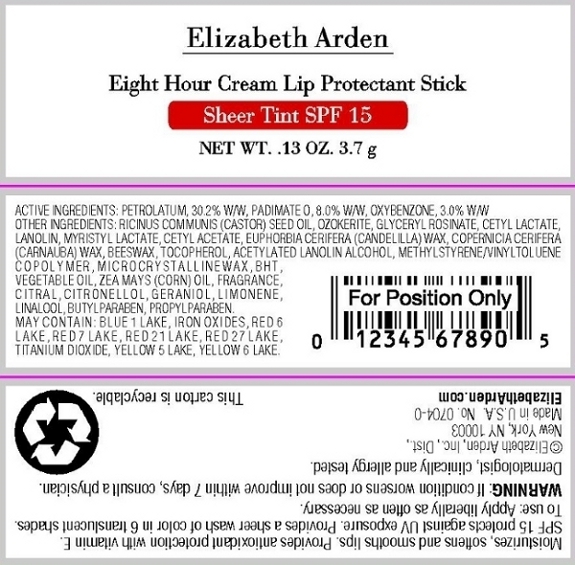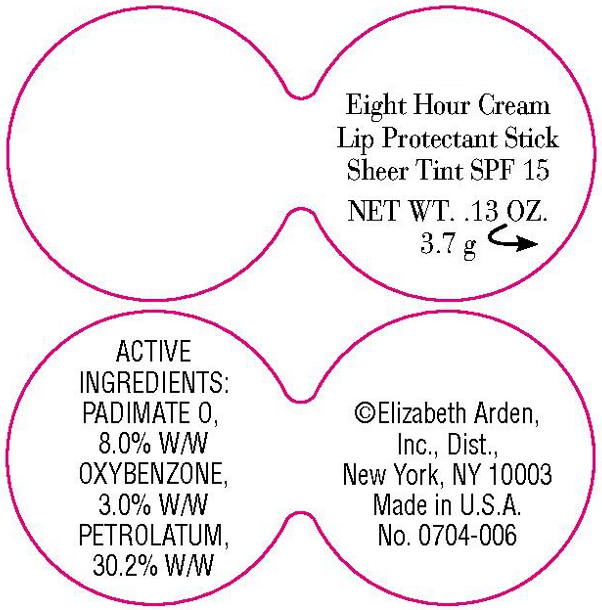 DRUG LABEL: Eight Hour Cream Lip Protectant Sheer Tint SPF 15 Chestnut
NDC: 67938-1410 | Form: STICK
Manufacturer: Elizabeth Arden, Inc
Category: otc | Type: HUMAN OTC DRUG LABEL
Date: 20110114

ACTIVE INGREDIENTS: PETROLATUM 1.117 g/3.7 g; PADIMATE O 0.296 g/3.7 g; OXYBENZONE 0.111 g/3.7 g
INACTIVE INGREDIENTS: CASTOR OIL; MYRISTYL LACTATE; CANDELILLA WAX; YELLOW WAX; MICROCRYSTALLINE WAX; BUTYLPARABEN; PROPYLPARABEN; BUTYLATED HYDROXYTOLUENE; ALPHA-TOCOPHEROL; CORN OIL

BL1410

DESCRIPTION

Moisturizes, softens and smooths lips. Provides antioxidant protection with vitamin E. SPF 15 protects against UV exposure. Provides a sheer wash of color in 6 translucent shades. Dermatologist, clinically and allergy tested.

INDICATIONS AND USAGE

To Use: Apply liberally as often as necessary.

WARNINGS

Warning: If condition worsens or does not improve within 7 days, consult a physician.

OTC - ACTIVE INGREDIENT

Active Ingredients: Petrolatum, 30.2% w/w, Padimate O, 8.0% w/w, Oxybenzone, 3.0% w/w.

INACTIVE INGREDIENT

Other Ingredients: Ozokerite, Ricinus Communis (Castor) Seed Oil, Glyceryl Rosinate, Cetyl Lactate, Lanolin Oil, Myristyl Lactate, Cetyl Acetate, Euphorbia Cerifera (Candelilla) Wax/Candelilla Cera/Cire De Candelilla, Copernicia Cerifera (Carnauba) Wax/Cer Carnauba/Cire De Carnauba, Beeswax/Cera Alba/Cire D'Abeille, Tocopherol, Acetylated Lanolin Alcohol, Methylstyrene/Vinyltoluene Copolymer, Microcrystalline Wax/Cera Microcristallina/Cire Microcristalline, BHT, Vegetable Oil/Olus/Huile Vegetale, Zea Mays (Corn) Oil, Citral Citronellol, Geraniol, Limonene, Linalool, Butylparaben, Propylparaben.

May Contain: Blue 1 Lake (CI 42090), Iron Oxides (CI 77491, CI 77499, CI 77492), Red 6 Lake (CI 15850), Red 7 Lake (CI 15850), Red 21 Lake (CI 45380), Red 27 Lake (CI 45410), Titanium Dioxide (CI 77891), Yellow 5 Lake (CI 19140), Yellow 6 Lake (CI15985).

DOSAGE & ADMINISTRATION

Apply to lips.

OTC - KEEP OUT OF REACH OF CHILDREN

Keep out of reach of children.

OTC - PURPOSE

SPF 15 protects against UV exposure.

OTC - WHEN USING

Note condition.